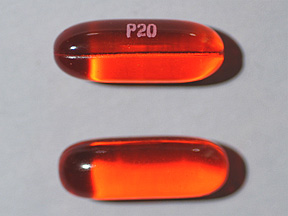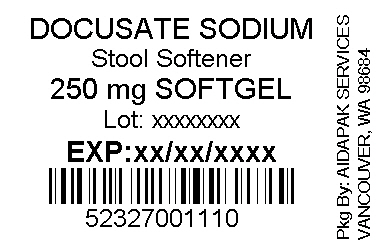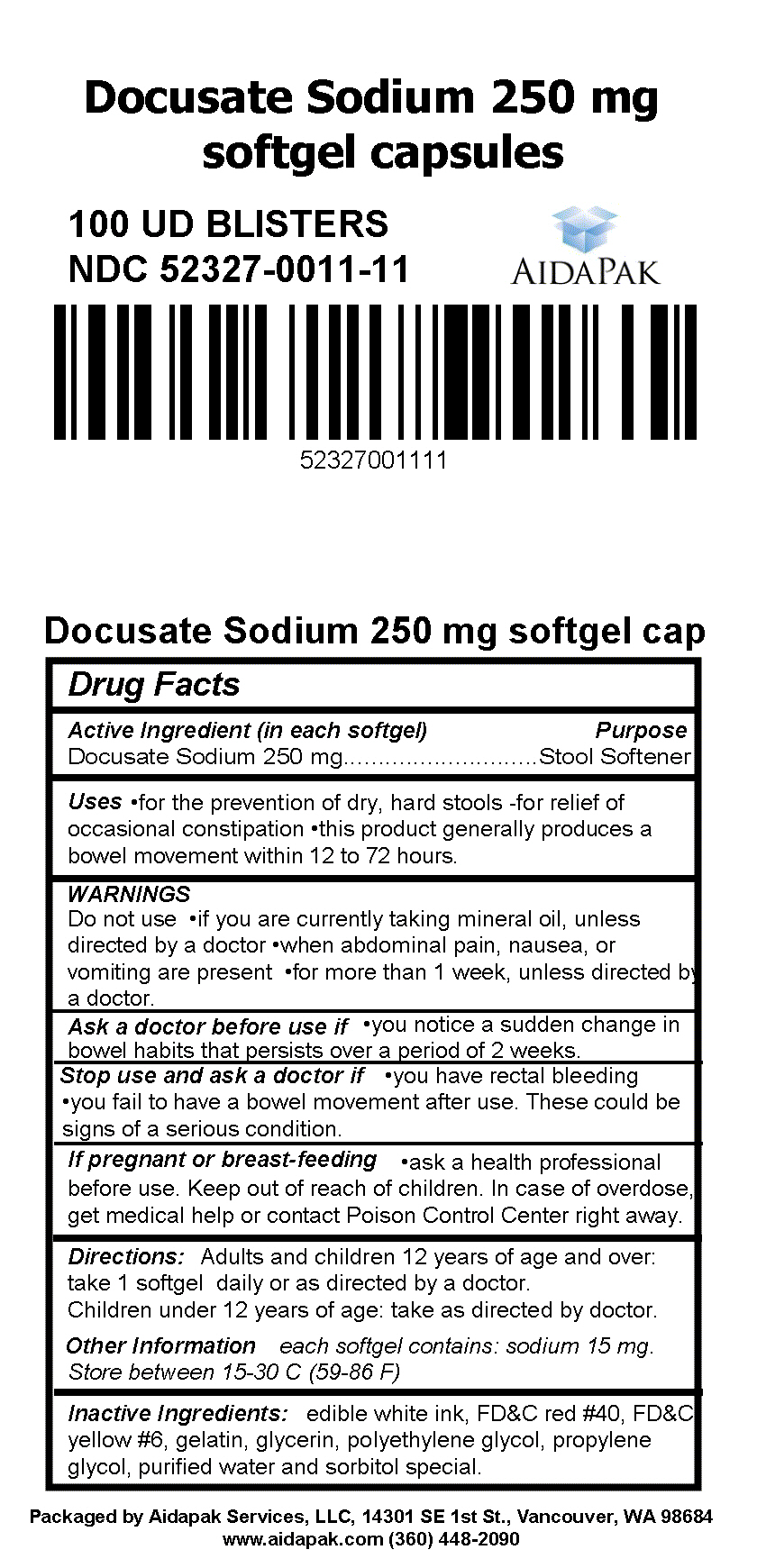 DRUG LABEL: EXTRA STRENGTH STOOL SOFTENER LAXATIVE
NDC: 52327-011 | Form: CAPSULE, LIQUID FILLED
Manufacturer: Aidapak Services, LLC
Category: otc | Type: HUMAN OTC DRUG LABEL
Date: 20141010

ACTIVE INGREDIENTS: DOCUSATE SODIUM 250 mg/250 mg
INACTIVE INGREDIENTS: FD&C RED NO. 40; FD&C YELLOW NO. 6; GELATIN; GLYCERIN; POLYETHYLENE GLYCOLS; PROPYLENE GLYCOL; WATER; SORBITOL

Docusate Sodium 250mg - Relabeled Product

Active Ingredient (in each softgel)

Docusate Sodium 250 mg

Purpose

Stool Softener

Uses:

•for the prevention of dry, hard stools

•for relief of occasional constipation

•this product generally produces a bowel movement within 12 to 72 hours.

Do not use

•if you are currently taking mineral oil, unless directed by a doctor

•when abdominal pain, nausea, or

vomiting are present

•for more than 1 week, unless directed by a doctor.

Ask a doctor before use if:

•you notice a sudden change in bowel habits that persists over a period of 2 weeks.

Stop use and ask a doctor if:

•you have rectal bleeding

•you fail to have a bowel movement after use. These could be signs of a serious condition.

PREGNANCY OR BREAST FEEDING

•ask a health professional before use. Keep out of reach of children. In case of overdose, get medical help or contact Poison Control Center right away.

Directions:

Adults and children 12 years of age and over:

take 1 softgel daily or as directed by a doctor.

Children under 12 years of age: take as directed by doctor.

Other Information:

each softgel contains: sodium 15 mg.

Store between 15-30 C (59-86 F)

INACTIVE INGREDIENT

edible white ink, FD&C red 40, FD&C yellow 6, gelatin, glycerin, polyethylene glycol, propylene glycol, purified water and sorbitol special.